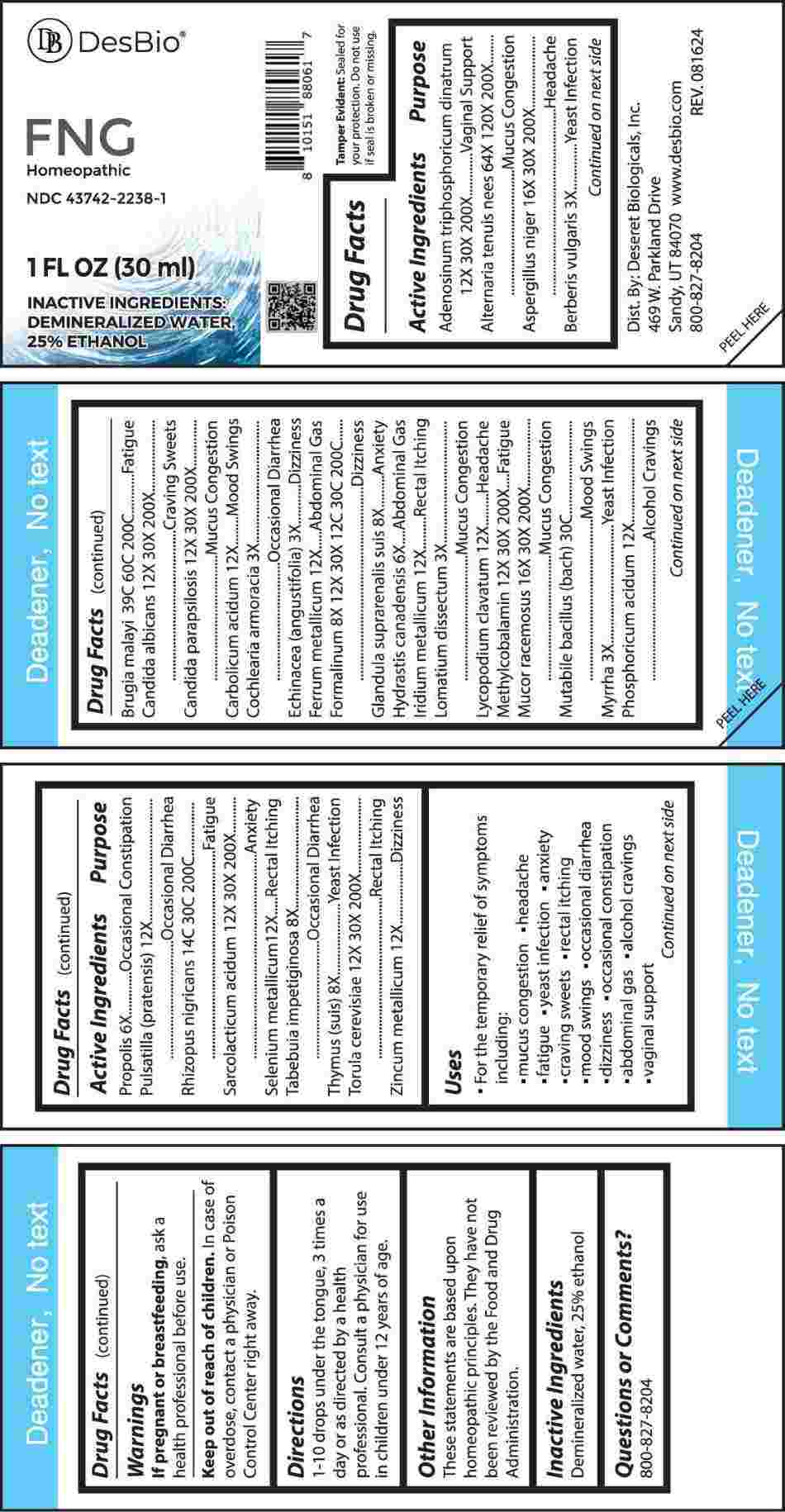 DRUG LABEL: FNG
NDC: 43742-2238 | Form: LIQUID
Manufacturer: Deseret Biologicals, Inc.
Category: homeopathic | Type: HUMAN OTC DRUG LABEL
Date: 20241120

ACTIVE INGREDIENTS: ADENOSINE TRIPHOSPHATE DISODIUM 12 [hp_X]/1 mL; ALTERNARIA ALTERNATA 64 [hp_X]/1 mL; ASPERGILLUS NIGER VAR. NIGER 16 [hp_X]/1 mL; BERBERIS VULGARIS ROOT BARK 3 [hp_X]/1 mL; BRUGIA MALAYI 39 [hp_C]/1 mL; CANDIDA ALBICANS 12 [hp_X]/1 mL; CANDIDA PARAPSILOSIS 12 [hp_X]/1 mL; PHENOL 12 [hp_X]/1 mL; HORSERADISH 3 [hp_X]/1 mL; ECHINACEA ANGUSTIFOLIA WHOLE 3 [hp_X]/1 mL; IRON 12 [hp_X]/1 mL; FORMALDEHYDE SOLUTION 8 [hp_X]/1 mL; SUS SCROFA ADRENAL GLAND 8 [hp_X]/1 mL; GOLDENSEAL 6 [hp_X]/1 mL; IRIDIUM 12 [hp_X]/1 mL; LOMATIUM DISSECTUM ROOT 3 [hp_X]/1 mL; LYCOPODIUM CLAVATUM SPORE 12 [hp_X]/1 mL; METHYLCOBALAMIN 12 [hp_X]/1 mL; MUCOR RACEMOSUS 16 [hp_X]/1 mL; ESCHERICHIA COLI 30 [hp_C]/1 mL; MYRRH 3 [hp_X]/1 mL; PHOSPHORIC ACID 12 [hp_X]/1 mL; PROPOLIS WAX 6 [hp_X]/1 mL; PULSATILLA PRATENSIS WHOLE 12 [hp_X]/1 mL; RHIZOPUS STOLONIFER 14 [hp_C]/1 mL; LACTIC ACID, L- 12 [hp_X]/1 mL; SELENIUM 12 [hp_X]/1 mL; TABEBUIA IMPETIGINOSA BARK 8 [hp_X]/1 mL; SUS SCROFA THYMUS 8 [hp_X]/1 mL; SACCHAROMYCES CEREVISIAE 12 [hp_X]/1 mL; ZINC 12 [hp_X]/1 mL
INACTIVE INGREDIENTS: WATER; ALCOHOL

DRUG FACTS:

ACTIVE INGREDIENTS:

Adenosinum Triphosphoricum Dinatrum 12X, 30X, 200X, Alternaria Tenuis Nees 64X, 120X, 200X, Aspergillus Niger 16X, 30X, 200X, Berberis Vulgaris 3X, Brugia Malayi 39C, 60C, 200C, Candida Albicans 12X, 30X, 200X, Candida Parapsilosis 12X, 30X, 200X, Carbolicum Acidum 12X, Cochlearia Armoracia 3X, Echinacea (Angustifolia) 3X, Ferrum Metallicum 12X, Formalinum 8X, 12X, 30X, 12C, 30C, 200C, Glandula Suprarenalis Suis 8X, Hydrastis Canadensis 6X, Iridium Metallicum 12X, Lomatium Dissectum 3X, Lycopodium Clavatum 12X, Methylcobalamin 12X, 30X, 200X, Mucor Racemosus 16X, 30X, 200X, Mutabile Bacillus (Bach) 30C, Myrrha 3X, Phosphoricum Acidum 12X, Propolis 6X, Pulsatilla (Pratensis) 12X, Rhizopus Nigricans 14C, 30C, 200C, Sarcolacticum Acidum 12X, 30X, 200X, Selenium Metallicum 12X, Tabebuia Impetiginosa 8X, Thymus (Suis) 8X, Torula Cerevisiae 12X, 30X, 200X, Zincum Metallicum 12X.

PURPOSE:

Adenosinum Triphosphoricum Dinatrum – Vaginal Support, Alternaria Tenuis Nees – Mucus Congestion, Aspergillus Niger - Headache, Berberis Vulgaris – Yeast infection, Brugia Malayi - Fatigue, Candida Albicans – Craving Sweets, Candida Parapsilosis – Mucus Congestion, Carbolicum Acidum – Mood Swings, Cochlearia Armoracia – Occasional Diarrhea, Echinacea (Angustifolia) - Dizziness, Ferrum Metallicum – Abdominal Gas, Formalinum - Dizziness, Glandula Suprarenalis Suis - Anxiety, Hydrastis Canadensis – Abdominal Gas, Iridium Metallicum – Rectal Itching, Lomatium Dissectum – Mucus Congestion, Lycopodium Clavatum - Headache, Methylcobalamin - Fatigue, Mucor Racemosus – Mucus Congestion, Mutabile Bacillus (Bach) – Mood Swings, Myrrha – Yeast Infections, Phosphoricum Acidum – Alcohol Cravings, Propolis – Occasional Constipation, Pulsatilla (Pratensis) – Occasional Diarrhea, Rhizopus Nigricans - Fatigue, Sarcolacticum Acidum - Anxiety, Selenium Metallicum – Rectal Itching, Tabebuia Impetiginosa – Occasional Diarrhea, Thymus (Suis) – Yeast Infections, Torula Cerevisiae – Rectal Itching, Zincum Metallicum - Dizziness

USES:

• For the temporary relief of symptoms including:

• mucous congestion • headache • fatigue • yeast infection

• anxiety • craving sweets • rectal itching • mood swings

• occasional diarrhea • dizziness • occasional constipation

• abdominal gas • alcohol cravings • vaginal support

These statements are based upon homeopathic principles. They have not been reviewed by the Food and Drug Administration.

WARNINGS:

If pregnant or breast-feeding, ask a health professional before use.

Keep out of reach of children. In case of overdose, contact a physician or Poison Control Center right away.

Tamper Evident: Sealed for your protection. Do not use if seal is broken or missing.

KEEP OUT OF REACH OF CHILDREN:

In case of overdose, contact a physician or Poison Control Center right away.

DIRECTIONS:

1-10 drops under the tongue, 3 times a day or as directed by a health professional. Consult a physician for use in children under 12 years of age.

INACTIVE INGREDIENTS:

Demineralized water, 25% ethanol

QUESTIONS:

Dist. By: Deseret Biologicals, Inc.
469 W. Parkland Drive
Sandy, UT 84070

www.desbio.com

800-827-8204

PACKAGE LABEL DISPLAY:

DesBio

FNG

Homeopathic
NDC 43742-2238-1

1 FL OZ (30 ml)